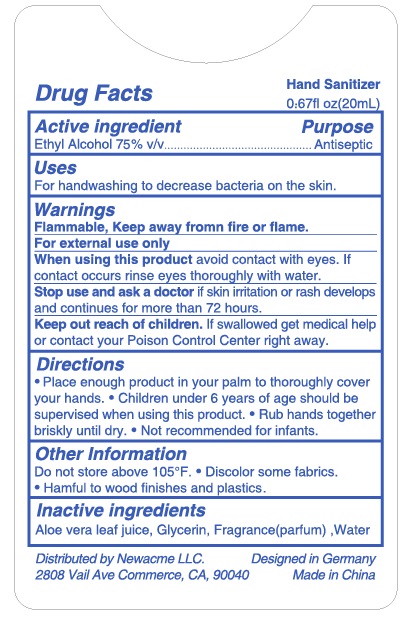 DRUG LABEL: Hand Sanitizer
NDC: 77753-003 | Form: SPRAY
Manufacturer: SHANDISHI Biological Technology Co., Ltd.
Category: otc | Type: HUMAN OTC DRUG LABEL
Date: 20200531

ACTIVE INGREDIENTS: ALCOHOL 75 mL/100 mL
INACTIVE INGREDIENTS: WATER; GLYCERIN; ALOE VERA LEAF

77753-003 Hand Sanitizer Alcohol Spray

Active Ingredient

Ethyl Alcohol 75%

Purpose

Antiseptic

Use

For handwashing to decrease bacteria on the skin.

WARNINGS

Flammable, Keep away fromn fire or flame.
For external use only
When using this product avoid contact with eyes. If
contact occurs rinse eyes thoroughly with water.
Stop use and ask a doctor if skin iritation or rash develops
and continues for more than 72 hours.

Keep out of reach of children
If swallowed , get medical help or contact a Poison Control Center right away

Directions

●Place enough product in your palm to thoroughly cover
your hands.●Children under 6 years of age should be
supervised when using this product.●Rub hands together
briskly until dry.●Not recommended for infants.

Inactive ingredients

Aloe vera leaf juice, Glycerin, Fragrance(parfum) ,Water